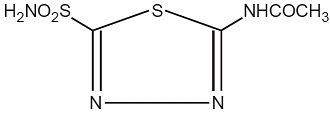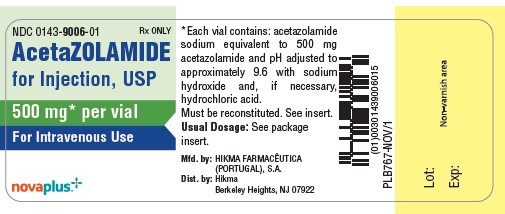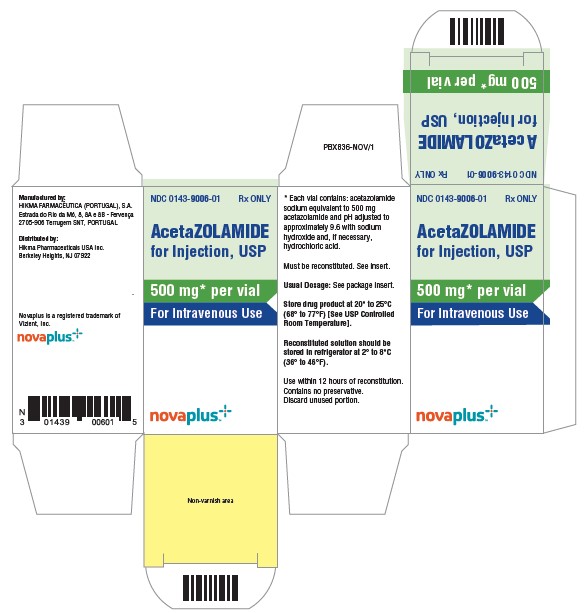 DRUG LABEL: AcetaZOLAMIDE
NDC: 0143-9006 | Form: INJECTION, POWDER, LYOPHILIZED, FOR SOLUTION
Manufacturer: Hikma Pharmaceuticals USA Inc.
Category: prescription | Type: HUMAN PRESCRIPTION DRUG LABEL
Date: 20251103

ACTIVE INGREDIENTS: ACETAZOLAMIDE SODIUM 500 mg/1 1
INACTIVE INGREDIENTS: SODIUM HYDROXIDE; HYDROCHLORIC ACID

AcetaZOLAMIDE for Injection USP

For Intravenous Use

Rx only

DESCRIPTION

Acetazolamide, an inhibitor of the enzyme carbonic anhydrase, is a white to faintly yellowish white crystalline, odorless powder, weakly acidic, very slightly soluble in water and slightly soluble in alcohol. The chemical name for acetazolamide is N-(5-Sulfamoyl-1,3,4-thiadiazol-2yl)-acetamide and has the following structural formula:

M.W. 222.24 C4H6N4O3S2

Acetazolamide for Injection, USP is available for intravenous use, and is supplied as a sterile powder requiring reconstitution. Each vial contains acetazolamide sodium equivalent to 500 mg of acetazolamide. The bulk solution is adjusted to pH 9.6 using sodium hydroxide and, if necessary, hydrochloric acid prior to lyophilization.

CLINICAL PHARMACOLOGY

Acetazolamide is a potent carbonic anhydrase inhibitor, effective in the control of fluid secretion (e.g., some types of glaucoma), in the treatment of certain convulsive disorders (e.g., epilepsy) and in the promotion of diuresis in instances of abnormal fluid retention (e.g., cardiac edema).

Acetazolamide is not a mercurial diuretic. Rather, it is a nonbacteriostatic sulfonamide possessing a chemical structure and pharmacological activity distinctly different from the bacteriostatic sulfonamides.

Acetazolamide is an enzyme inhibitor that acts specifically on carbonic anhydrase, the enzyme that catalyzes the reversible reaction involving the hydration of carbon dioxide and the dehydration of carbonic acid. In the eye, this inhibitory action of acetazolamide decreases the secretion of aqueous humor and results in a drop in intraocular pressure, a reaction considered desirable in cases of glaucoma and even in certain nonglaucomatous conditions. Evidence seems to indicate that acetazolamide has utility as an adjuvant in the treatment of certain dysfunctions of the central nervous system (e.g., epilepsy). Inhibition of carbonic anhydrase in this area appears to retard abnormal, paroxysmal, excessive discharge from central nervous system neurons. The diuretic effect of acetazolamide is due to its action in the kidney on the reversible reaction involving hydration of carbon dioxide and dehydration of carbonic acid.

The result is renal loss of HCO3 ion, which carries out sodium, water, and potassium. Alkalinization of the urine and promotion of diuresis are thus effected. Alteration in ammonia metabolism occurs due to increased reabsorption of ammonia by the renal tubules as a result of urinary alkalinization.

INDICATIONS AND USAGE

For adjunctive treatment of: edema due to congestive heart failure; drug-induced edema; centrencephalic epilepsies (petit mal, unlocalized seizures); chronic simple (open-angle) glaucoma, secondary glaucoma, and preoperatively in acute angle-closure glaucoma where delay of surgery is desired in order to lower intraocular pressure.

CONTRAINDICATIONS

Hypersensitivity to acetazolamide or any excipients in the formulation. Since acetazolamide is a sulfonamide derivative, cross sensitivity between acetazolamide, sulfonamides and other sulfonamide derivatives is possible.

Acetazolamide therapy is contraindicated in situations in which sodium and/or potassium blood serum levels are depressed, in cases of marked kidney and liver disease or dysfunction, in suprarenal gland failure, and in hyperchloremic acidosis. It is contraindicated in patients with cirrhosis because of the risk of development of hepatic encephalopathy.

Long-term administration of acetazolamide is contraindicated in patients with chronic noncongestive angle-closure glaucoma since it may permit organic closure of the angle to occur while the worsening glaucoma is masked by lowered intraocular pressure.

WARNINGS

Fatalities have occurred, although rarely, due to severe reactions to sulfonamides including Stevens-Johnson syndrome, toxic epidermal necrolysis, fulminant hepatic necrosis, agranulocytosis, aplastic anemia, and other blood dyscrasias. Sensitizations may recur when a sulfonamide is readministered irrespective of the route of administration. If signs of hypersensitivity or other serious reactions occur, discontinue use of this drug.

Caution is advised for patients receiving concomitant high-dose aspirin and acetazolamide, as anorexia, tachypnea, lethargy, coma and death have been reported.

PRECAUTIONS

General

Increasing the dose does not increase the diuresis and may increase the incidence of drowsiness and/or paresthesia. Increasing the dose often results in a decrease in diuresis. Under certain circumstances, however, very large doses have been given in conjunction with other diuretics in order to secure diuresis in complete refractory failure.

Choroidal effusion and choroidal detachment have been reported after the use of acetazolamide in the post-operative period following ophthalmic surgery. Discontinue Acetazolamide for Injection if choroidal effusion and/or choroidal detachment is suspected.

Information for Patients

Adverse reactions common to all sulfonamide derivatives may occur: anaphylaxis, fever, rash (including erythema multiforme, Stevens-Johnson syndrome, toxic epidermal necrolysis), crystalluria, renal calculus, bone marrow depression, thrombocytopenic purpura, hemolytic anemia, leukopenia, pancytopenia and agranulocytosis. Precaution is advised for early detection of such reactions and the drug should be discontinued and appropriate therapy instituted.

In patients with pulmonary obstruction or emphysema where alveolar ventilation may be impaired, acetazolamide which may precipitate or aggravate acidosis, should be used with caution.

Caution is advised for patients receiving concomitant high-dose aspirin and acetazolamide, as anorexia, tachypnea, lethargy, coma and death have been reported (see WARNINGS).

Laboratory Tests

To monitor for hematologic reactions common to all sulfonamides, it is recommended that a baseline CBC and platelet count be obtained on patients prior to initiating acetazolamide therapy and at regular intervals during therapy. If significant changes occur, early discontinuance and institution of appropriate therapy are important. Periodic monitoring of serum electrolytes is recommended.

Carcinogenesis, Mutagenesis, Impairment of Fertility

Long-term studies in animals to evaluate the carcinogenic potential of acetazolamide have not been conducted. In a bacterial mutagenicity assay, acetazolamide was not mutagenic when evaluated with and without metabolic activation.

The drug had no effect on fertility when administered in the diet to male and female rats at a daily intake of up to 4 times the recommended human dose of 1000 mg in a 50 kg individual.

Pregnancy:

Teratogenic effects: Pregnancy Category C

Acetazolamide, administered orally or parenterally, has been shown to be teratogenic (defects of the limbs) in mice, rats, hamsters and rabbits. There are no adequate and well-controlled studies in pregnant women. Acetazolamide should be used in pregnancy only if the potential benefit justifies the potential risk to the fetus.

Nursing Mothers

Because of the potential for serious adverse reaction in nursing infants from acetazolamide, a decision should be made whether to discontinue nursing or to discontinue the drug taking into account the importance of the drug to the mother.

Pediatric Use

The safety and effectiveness of acetazolamide in children have not been established.

ADVERSE REACTIONS

Adverse reactions, occurring most often early in therapy, include paresthesias, particularly a “tingling” feeling in the extremities, hearing dysfunction or tinnitus, loss of appetite, taste alteration and gastrointestinal disturbances such as nausea, vomiting and diarrhea; polyuria, and occasional instances of drowsiness and confusion.

Metabolic acidosis and electrolyte imbalance may occur.

Transient myopia has been reported. This condition invariably subsides upon diminution or discontinuance of the medication.

Other occasional adverse reactions include urticaria, melena, hematuria, glycosuria, hepatic insufficiency, flaccid paralysis, photosensitivity and convulsions. Also see PRECAUTIONS: Information for Patients for possible reactions common to sulfonamide derivatives. Fatalities have occurred although rarely, due to severe reactions to sulfonamides including Stevens-Johnson syndrome, toxic epidermal necrolysis, fulminant hepatic necrosis, agranulocytosis, aplastic anemia and other blood dyscrasias (see WARNINGS).

OVERDOSAGE

No data are available regarding acetazolamide overdosage in humans as no cases of acute poisoning with this drug have been reported. Animal data suggest that acetazolamide is remarkably nontoxic. No specific antidote is known. Treatment should be symptomatic and supportive.

Electrolyte imbalance, development of an acidotic state, and central nervous effects might be expected to occur. Serum electrolyte levels (particularly potassium) and blood pH levels should be monitored.

Supportive measures are required to restore electrolyte and pH balance. The acidotic state can usually be corrected by the administration of bicarbonate.

Despite its high intraerythrocytic distribution and plasma protein binding properties, acetazolamide may be dialyzable. This may be particularly important in the management of acetazolamide overdosage when complicated by the presence of renal failure.

DOSAGE AND ADMINISTRATION

Preparation and Storage of Parenteral Solution

Each 500 mg vial containing sterile acetazolamide sodium should be reconstituted with at least 5 mL of Sterile Water for Injection prior to use. Reconstituted solutions retain their physical and chemical properties for 3 days under refrigeration at 2° to 8°C (36° to 46°F), or 12 hours at room temperature 20° to 25°C (68° to 77°F). Contains no preservative. The direct intravenous route of administration is preferred. Intramuscular administration is not recommended.

Glaucoma

Acetazolamide should be used as an adjunct to the usual therapy. The dosage employed in the treatment of chronic simple (open-angle) glaucoma ranges from 250 mg to 1 g of acetazolamide per 24 hours, usually in divided doses for amounts over 250 mg. It has usually been found that a dosage in excess of 1 g per 24 hours does not produce an increased effect. In all cases, the dosage should be adjusted with careful individual attention both to symptomatology and ocular tension. Continuous supervision by a physician is advisable.

In treatment of secondary glaucoma and in the preoperative treatment of some cases of acute congestive (closed-angle) glaucoma, the preferred dosage is 250 mg every four hours, although some cases have responded to 250 mg twice daily on short-term therapy. In some acute cases, it may be more satisfactory to administer an initial dose of 500 mg followed by 125 or 250 mg every four hours depending on the individual case. Intravenous therapy may be used for rapid relief of ocular tension in acute cases. A complementary effect has been noted when acetazolamide has been used in conjunction with miotics or mydriatics as the case demanded.

Epilepsy

It is not clearly known whether the beneficial effects observed in epilepsy are due to direct inhibition of carbonic anhydrase in the central nervous system or whether they are due to the slight degree of acidosis produced by the divided dosage. The best results to date have been seen in petit mal in children. Good results, however, have been seen in patients, both children and adult, in other types of seizures such as grand mal, mixed seizure patterns, myoclonic jerk patterns, etc. The suggested total daily dose is 8 to 30 mg per kg in divided doses. Although some patients respond to a low dose, the optimum range appears to be from 375 to 1000 mg daily. However, some investigators feel that daily doses in excess of 1 g do not produce any better results than a 1 g dose. When acetazolamide is given in combination with other anticonvulsants, it is suggested that the starting dose should be 250 mg once daily in addition to the existing medications. This can be increased to levels as indicated above.

The change from other medications to acetazolamide should be gradual and in accordance with usual practice in epilepsy therapy.

Congestive Heart Failure

For diuresis in congestive heart failure, the starting dose is usually 250 to 375 mg once daily in the morning (5 mg per kg). If, after an initial response, the patient fails to continue to lose edema fluid, do not increase the dose but allow for kidney recovery by skipping medication for a day.

Acetazolamide yields best diuretic results when given on alternate days, or for two days alternating with a day of rest.

Failures in therapy may be due to overdosage or too frequent dosage. The use of acetazolamide does not eliminate the need for other therapy such as digitalis, bed rest, and salt restriction.

Drug-Induced Edema

Recommended dosage is 250 to 375 mg of acetazolamide once a day for one or two days, alternating with a day of rest.

Note: The dosage recommendations for glaucoma and epilepsy differ considerably from those for congestive heart failure, since the first two conditions are not dependent upon carbonic anhydrase inhibition in the kidney which requires intermittent dosage if it is to recover from inhibitory effect of the therapeutic agent.

Parenteral drug products should be inspected visually for particulate matter and discoloration prior to administration, whenever solution and container permit.

HOW SUPPLIED

Acetazolamide for Injection, USP (lyophilized) powder.

NDC 0143-9006-01 500 mg Vial

Store drug product at 20° to 25°C (68° to 77°F) [See USP Controlled Room Temperature].

Reconstituted solution should be stored in refrigerator at 2° to 8°C (36° to 46°F). Use within 12 hours of reconstitution.

Contains no preservative. Discard unused portion.

To report SUSPECTED ADVERSE REACTIONS, contact Hikma Pharmaceuticals USA Inc. at 1-877-845-0689, or the FDA at 1-800-FDA-1088 or www.fda.gov/medwatch.

For Product Inquiry call 1-877-845-0689.

Manufactured by:

HIKMA FARMACÊUTICA (PORTUGAL), S.A.

Estrada do Rio da Mó, 8, 8A e 8B – Fervença – 2705-906 Terrugem SNT, PORTUGAL

Distributed by:

Hikma Pharmaceuticals USA Inc.

Berkeley Heights, NJ 07922
Novaplus is a registered trademark of Vizient, Inc.

novaplus+

Revised February 2025

PIN575-NOV/3

Vial Principal Display Panel

NDC 0143-9006-01 Rx ONLY

AcetaZOLAMIDE for Injection, USP

500 mg* per vial

For Intravenous Use

Carton Principal Display Panel

NDC 0143-9006-01 Rx ONLY

AcetaZOLAMIDE for Injection, USP

500 mg* per vial

For Intravenous Use